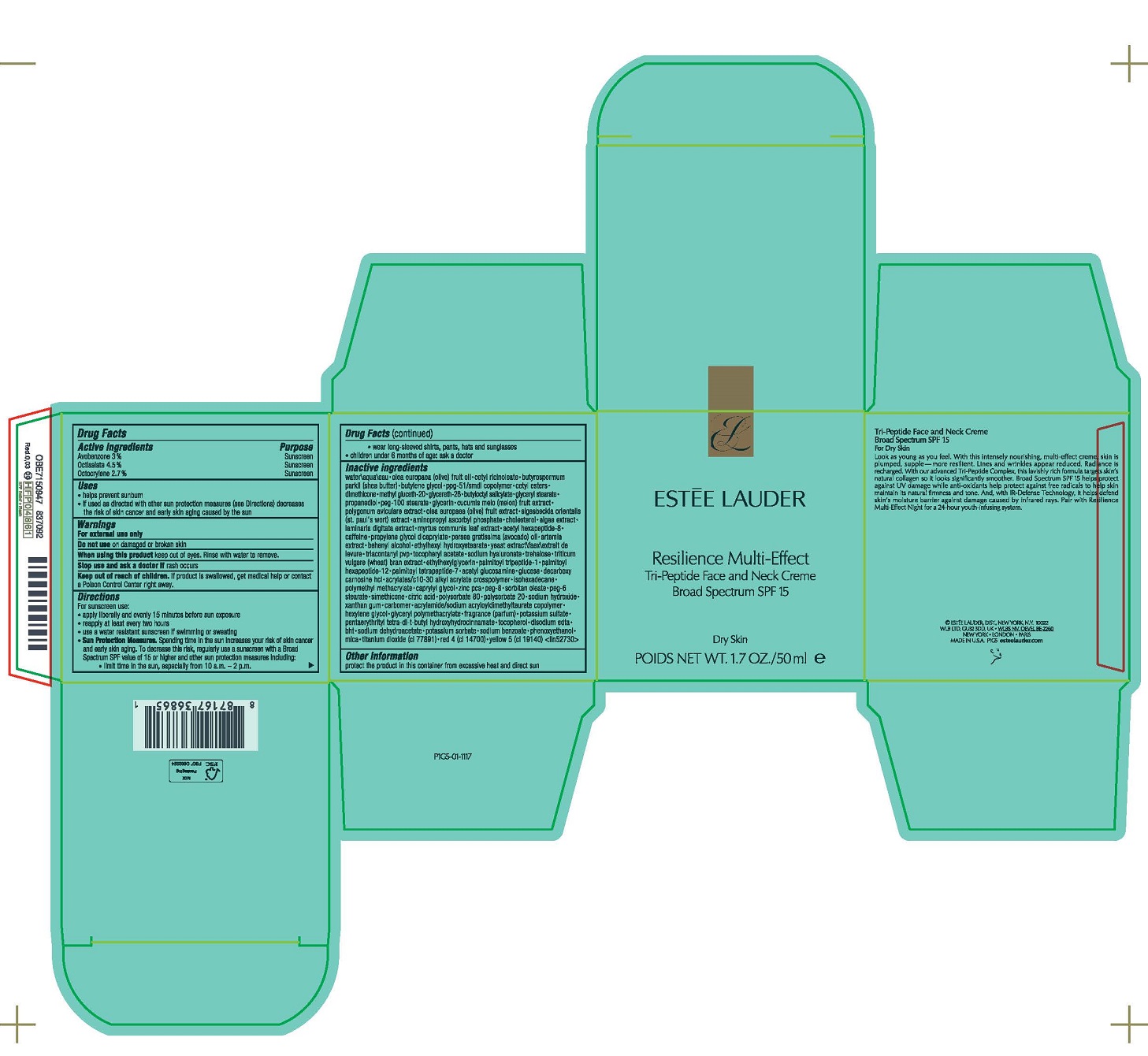 DRUG LABEL: RESILIENCE MULTI-EFFECT TRI-PEPTIDE FACE AND NECK CREME BROAD SPECTRUM SPF 15 dry skin
NDC: 11559-053 | Form: CREAM
Manufacturer: ESTEE LAUDER INC
Category: otc | Type: HUMAN OTC DRUG LABEL
Date: 20231027

ACTIVE INGREDIENTS: AVOBENZONE 0.03 g/1 mL; OCTISALATE 0.045 g/1 mL; OCTOCRYLENE 0.027 g/1 mL
INACTIVE INGREDIENTS: WATER; OLIVE OIL; CETYL RICINOLEATE; SHEA BUTTER; BUTYLENE GLYCOL; PPG-51/SMDI COPOLYMER; CETYL ESTERS WAX; DIMETHICONE; METHYL GLUCETH-20; GLYCERETH-26; BUTYLOCTYL SALICYLATE; GLYCERYL MONOSTEARATE; PROPANEDIOL; PEG-100 STEARATE; MUSKMELON; AMINOPROPYL ASCORBYL PHOSPHATE; CHOLESTEROL; GLYCERIN; ACETYL HEXAPEPTIDE-8; CAFFEINE; PROPYLENE GLYCOL DICAPRYLATE; AVOCADO OIL; DOCOSANOL; ETHYLHEXYL HYDROXYSTEARATE; TRICONTANYL POVIDONE; HYALURONATE SODIUM; TREHALOSE; ETHYLHEXYLGLYCERIN; N-ACETYLGLUCOSAMINE; DECARBOXY CARNOSINE HYDROCHLORIDE; ISOHEXADECANE; POLY(METHYL METHACRYLATE; 450000 MW); CAPRYLYL GLYCOL; ZINC PIDOLATE; CITRIC ACID MONOHYDRATE; POLYSORBATE 80; SODIUM HYDROXIDE; XANTHAN GUM; CARBOMER HOMOPOLYMER, UNSPECIFIED TYPE; HEXYLENE GLYCOL; POTASSIUM SULFATE; PENTAERYTHRITOL TETRAKIS(3-(3,5-DI-TERT-BUTYL-4-HYDROXYPHENYL)PROPIONATE); EDETATE DISODIUM ANHYDROUS; BUTYLATED HYDROXYTOLUENE; SODIUM DEHYDROACETATE; PHENOXYETHANOL; MICA; FD&C RED NO. 4; TITANIUM DIOXIDE; FD&C YELLOW NO. 5; MYRTUS COMMUNIS LEAF; .ALPHA.-TOCOPHEROL ACETATE; WHEAT BRAN; SORBITAN MONOOLEATE; POLYSORBATE 20; POLYGONUM AVICULARE TOP; LAMINARIA DIGITATA; ACRYLATES/C10-30 ALKYL ACRYLATE CROSSPOLYMER (60000 MPA.S); PEG-6 STEARATE; TOCOPHEROL; POTASSIUM SORBATE; PALMITOYL TRIPEPTIDE-1; PALMITOYL TETRAPEPTIDE-7; POLYETHYLENE GLYCOL 400; SODIUM BENZOATE; PALMITOYL HEXAPEPTIDE-12; PORPHYRIDIUM PURPUREUM; BLACK OLIVE; SIGESBECKIA ORIENTALIS FLOWERING TOP; YEAST, UNSPECIFIED

RESILIENCE MULTI-EFFECT TRI-PEPTIDE FACE AND NECK CREME BROAD SPECTRUM SPF 15 dry skin

Drug Facts

ACTIVE INGREDIENT

Active ingredients | Purpose
Avobenzone 3.0% | Sunscreen
Octisalate 4.5% | Sunscreen
Octocrylene 2.7% | Sunscreen

Uses

- helps prevent sunburn
- if used as directed with other sun protection measures (see Directions) decreases the risk of skin cancer and early skin aging caused by the sun

Warnings

For external use only

Do not use on damaged or broken skin

When using this product keep out of eyes. Rinse with water to remove.

Stop use and ask a doctor if rash occurs

Keep out of reach of children. If product is swallowed, get medical help or contact a Poison Control Center right away.

Directions

For sunscreen use:

- apply liberally and evenly 15 minutes before sun exposure
- reapply at least every two hours
- use a water resistant sunscreen if swimming or sweating
- Sun Protection Measures. Spending time in the sun increases your risk of skin cancer and early skin aging. To decrease this risk, regularly use a sunscreen with a Broad Spectrum SPF value of 15 or higher and other sun protection measures including:
  - limit time in the sun, especially from 10 a.m. – 2 p.m.
  - wear long-sleeved shirts, pants, hats and sunglasses
- children under 6 months of age: ask a doctor

Inactive ingredients

water\aqua\eau • olea europaea (olive) fruit oil • cetyl ricinoleate • butyrospermum parkii (shea butter) • butylene glycol • ppg-51/smdi copolymer • cetyl esters • dimethicone • methyl gluceth-20 • glycereth-26 • butyloctyl salicylate • glyceryl stearate • propanediol • peg-100 stearate • cucumis melo (melon) fruit extract • polygonum aviculare extract • triticum vulgare (wheat bran) extract • olea europaea (olive) fruit extract • sigesbeckia orientalis (st. paul's wort) extract • aminopropyl ascorbyl phosphate • cholesterol • algae extract • laminaria digitata extract • myrtus communis leaf extract • glycerin • trifluoroacetyl tripeptide-2 • acetyl hexapeptide-8 • caffeine • propylene glycol dicaprylate • persea gratissima (avocado) oil • artemia extract • behenyl alcohol • ethylhexyl hydroxystearate • triacontanyl pvp • tocopheryl acetate • sodium hyaluronate • trehalose • ethylhexylglycerin • fragrance (parfum) • acetyl glucosamine • tetradecyl aminobutyroylvalylaminobutyric urea trifluoroacetate • decarboxy carnosine hcl • acrylates/c10-30 alkyl acrylate crosspolymer • isohexadecane • polymethyl methacrylate • caprylyl glycol • zinc pca • simethicone • citric acid • polysorbate 80 • yeast extract\faex\extrait de levure • sodium hydroxide • xanthan gum • carbomer • acrylamide/sodium acryloyldimethyltaurate copolymer • hexylene glycol • potassium sulfate • pentaerythrityl tetra-di-t-butyl hydroxyhydrocinnamate • dextran • disodium edta • bht • sodium dehydroacetate • phenoxyethanol • mica • red 4 (ci 14700) • titanium dioxide (ci 77891) • yellow 5 (ci 19140) <iln44780>

Other information

protect the product in this container from excessive heat and direct sun

PRINCIPAL DISPLAY PANEL - 50 ml Jar Carton

ESTĒE LAUDER

Resilience Multi-Effect
Tri-Peptide Face and Neck Creme
Broad Spectrum SPF 15

Dry Skin

NET WT. 1.7 OZ./50 ml e